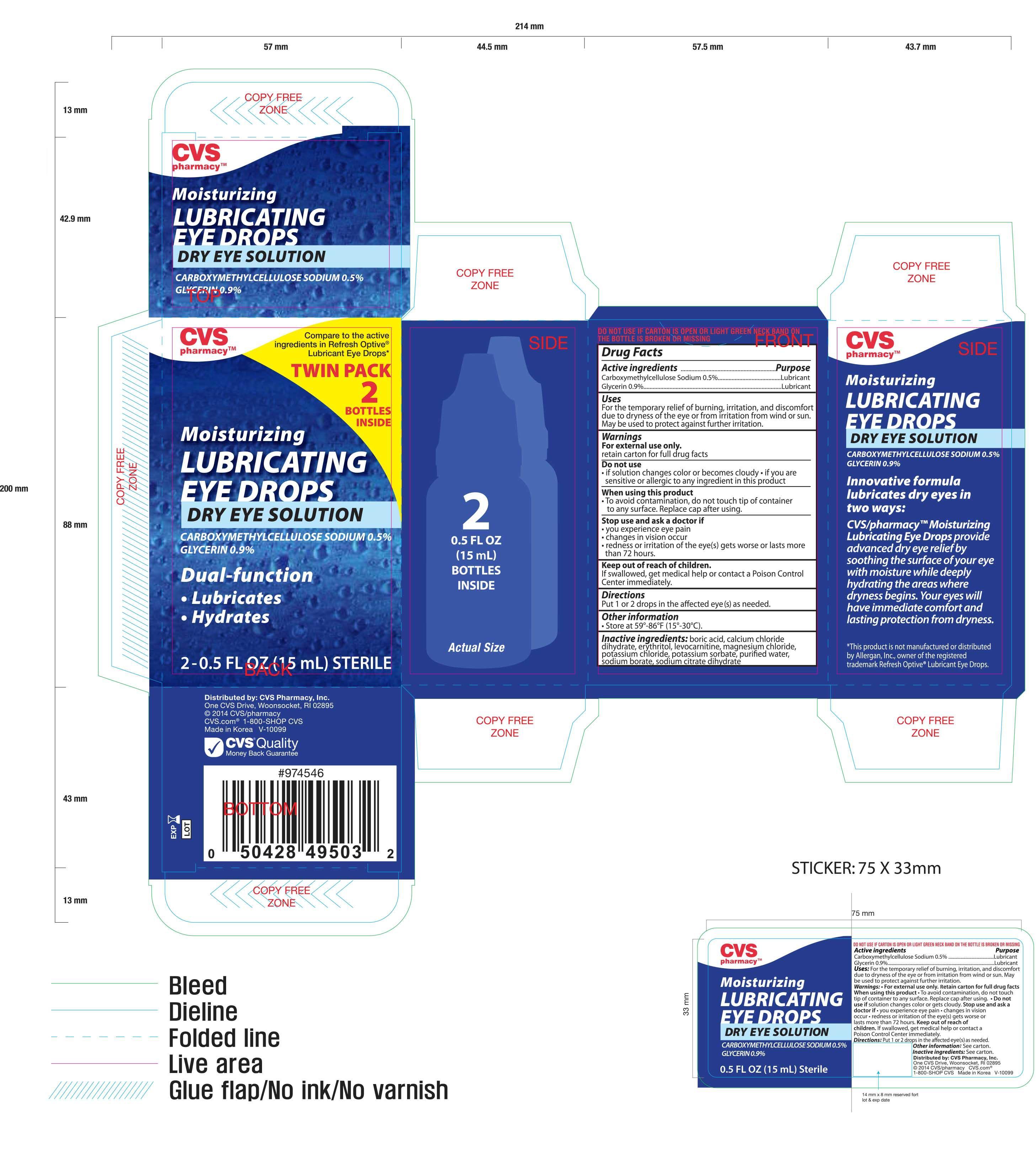 DRUG LABEL: CVS Moisturizing Lubricating Eye Twin Pack
NDC: 59779-495 | Form: SOLUTION/ DROPS
Manufacturer: CVS Pharmacy, Inc.
Category: otc | Type: HUMAN OTC DRUG LABEL
Date: 20140710

ACTIVE INGREDIENTS: CARBOXYMETHYLCELLULOSE SODIUM 5 mg/1 mL; GLYCERIN 9 mg/1 mL
INACTIVE INGREDIENTS: BORIC ACID; CALCIUM CHLORATE DIHYDRATE; ERYTHRITOL; LEVOCARNITINE; MAGNESIUM CHLORIDE; POTASSIUM CHLORIDE; POTASSIUM SORBATE; WATER; SODIUM BORATE

ACTIVE INGREDIENT

Active ingredients..................................................... Purpose

Carboxymethylcellulose Sodium 0.5%.......................... Lubricant

Glycerin 0.9%........................................................... Lubricant

Uses

For the temporary relief of burning, irritation, and discomfort due to dryness of the eye or from irritation from wind or sun. May be used to protect against further irritation.

Warnings

For external use only.

retain carton for full drug facts

Do not use

- if solution changes color or becomes cloudy
- if you are sensitive or allergic to any ingredient in this product

When using this product

- To avoid contamination, do not touch tip of container to any surface. Replace cap after using.

Stop use and ask a doctor if

- you experience eye pain
- changes in vision occur
- redness or irritation of the eye(s) gets worse or lasts more than 72 hours

KEEP OUT OF REACH OF CHILDREN

If swallowed, get medical help or contact a Poison Control Center immediately

Directions

Put 1 or 2 drops in the affected eye(s) as needed

STORAGE AND HANDLING

- Store at 59°-86°F (15°-30°C)

INACTIVE INGREDIENT

Inactive ingredients: boric acid, calcium chloride, dihydrate, erythritol, levocarnitine, magnesium chloride, potassium chloride, potassium sorbate, purified water, sodium borate, sodium citrate dihydrate

DOSAGE AND ADMINISTRATION

Distributed by:

CVS Pharmacy, Inc.

One CVS Drive

Woonsocket, RI 02895